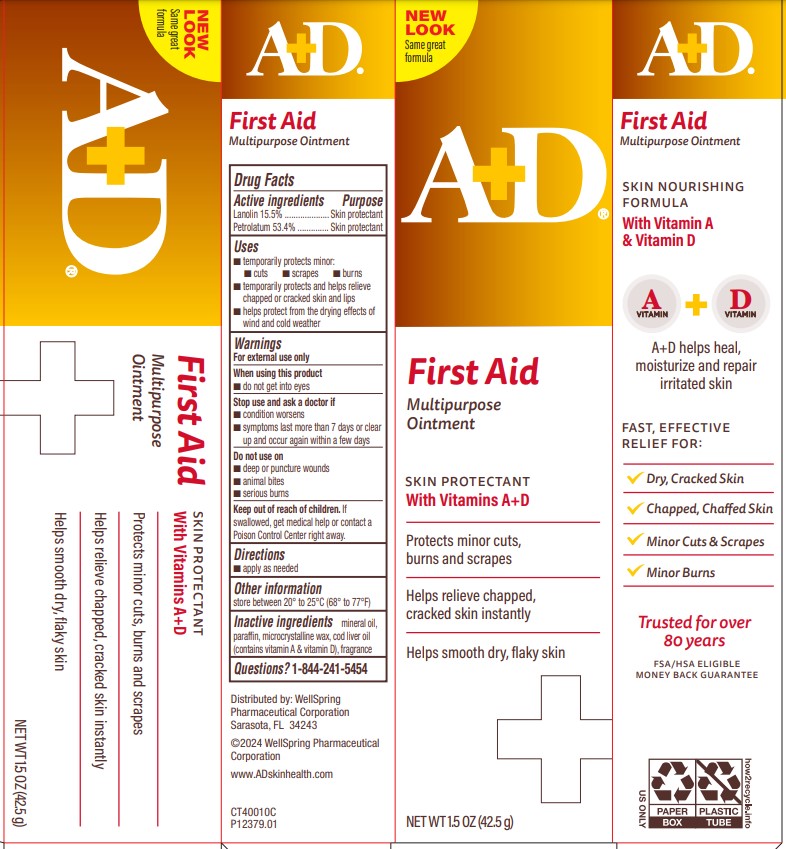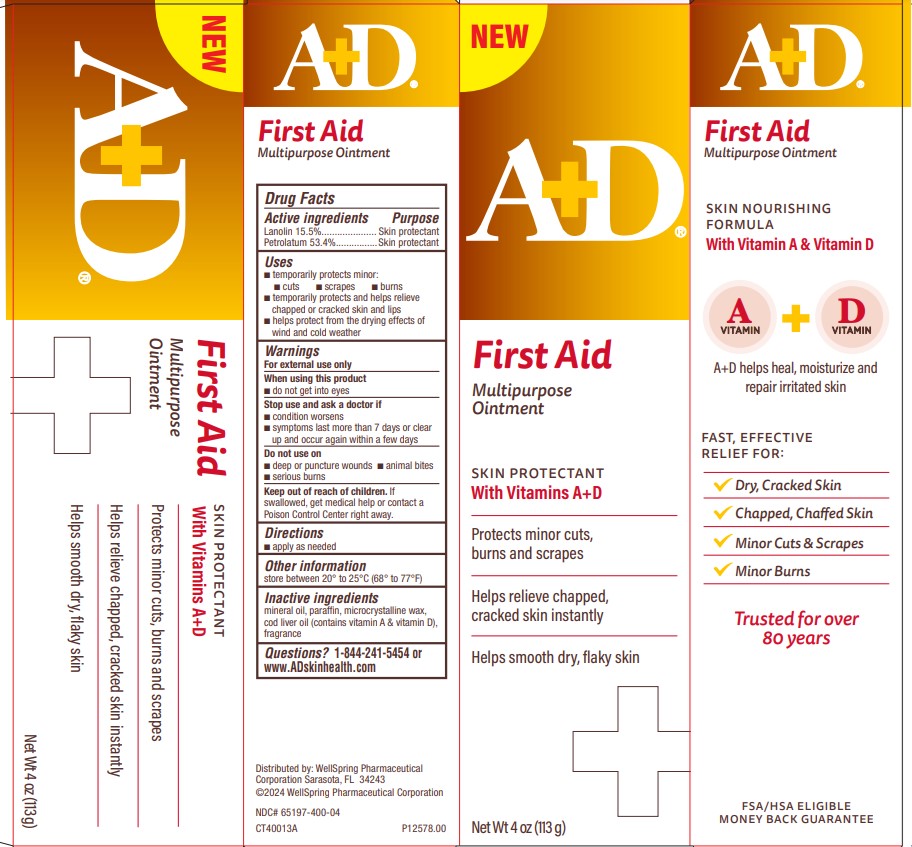 DRUG LABEL: AD First Aid Multipurpose
NDC: 65197-400 | Form: OINTMENT
Manufacturer: WellSpring Pharmaceutical Corporation
Category: otc | Type: HUMAN OTC DRUG LABEL
Date: 20240201

ACTIVE INGREDIENTS: PETROLATUM 53.4 g/100 g; LANOLIN 15.5 g/100 g
INACTIVE INGREDIENTS: COD LIVER OIL; LIGHT MINERAL OIL; MICROCRYSTALLINE WAX; PARAFFIN

A+D Treat Diaper Rash Cream with Dimethicone and Zinc Oxide

Active Ingredients

Lanolin 15.5%

Petrolatum 53.4%

Purpose

Skin protectant

Skin protectant

Uses

- temporarily protects minor:
  - cuts
  - scrapes
  - burns
- temporarily protects and helps relieve chapped or cracked skin and lips
- helps protect from the drying effects of wind and cold weather

Warnings

For external use only

When using this product

- do not get into eyes

Stop use and ask a doctor if

- condition worsens
- symptoms last more than 7 days or clear up and occur again within a few days

Do not use on

- deep or puncture wounds
- animal bites
- serious burns

Keep out of reach of children

If swallowed, get medical help or contact a Poison Control Center right away.

Directions

- apply as needed

Other information

store between 20° to 25°C (68° to 77°F)

Inactive ingredients

cod liver oil (contains vitamin A & vitamin D), fragrance, light mineral oil, microcrystalline wax, paraffin

Questions?

1-844-241-5454

Distributed by:

WellSpring Pharmaceutical Corporation
Sarasota, FL 34243

© 2023 WellSpring Pharmaceutical Corporation

www.ADskinhealth.com

PACKAGE LABEL. PRINCIPAL DISPLAY PANEL

A+D FIRST AID

Trusted for over 80 years

A+D® provides gentle, effective solutions to protect your skin.

MINOR CUTS, BURNS & SCRAPES

DRY, CHAPPED OR CRACKED SKIN

MULTIPURPOSE OINTMENT

Skin Protectant with Vitamins A+D

Protects minor cuts, burns, and scrapes

Helps relieve chapped, cracked skin

Helps smooth dry, flaky skin

NET WT 1.5 OZ (42.5 g)

AD first Aid 1.5oz

NET WT 4 OZ (113 g)

AD First Aid 4oz